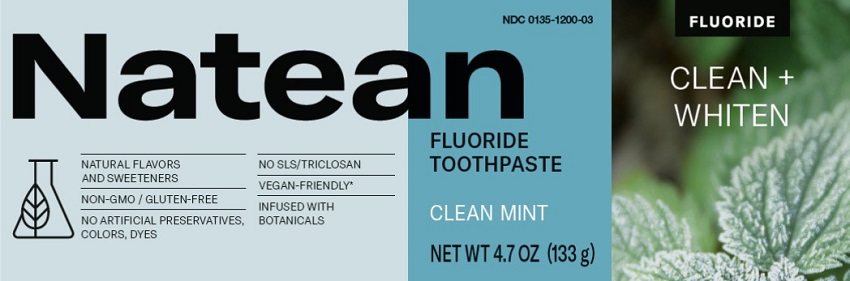 DRUG LABEL: NATEAN

NDC: 0135-1200 | Form: PASTE
Manufacturer: Haleon US Holdings LLC
Category: otc | Type: HUMAN OTC DRUG LABEL
Date: 20240319

ACTIVE INGREDIENTS: SODIUM FLUORIDE 1.5 mg/1 g
INACTIVE INGREDIENTS: WATER; HYDRATED SILICA; SORBITOL; GLYCERIN; COCAMIDOPROPYL BETAINE; SODIUM COCOYL GLUTAMATE; XANTHAN GUM; REBAUDIOSIDE A; MALTODEXTRIN; BROMELAINS; PAPAIN

Drug Facts

Active ingredient

Sodium fluoride 0.25% (0.15% w/v fluoride ion)

Purpose

Anticavity

Use

- aids in the prevention of dental cavities.

Warnings

When using this product,if irritation occurs discontinue use.

Directions

- adults and children 12 years of age and older:
  - brush teeth thoroughly, preferably after each meal or at least twice a day, and not more than 3 times a day, or as recommended by a dentist or doctor. Minimize swallowing. Spit out after brushing.
- Children under 12 years of age:Consult a dentist or doctor

Other information

- do not store above 25°C (77F°)

Inactive ingredients

water, hydrated silica, sorbitol, glycerin, cocamidopropyl betaine, sodium cocoyl glutamate, flavor, xanthan gum, rebaudioside A, maltodextrin, bromelain, papain

Questions or comments?

1-800-733-5879

Additional Information

ALWAYS FOLLOW THE LABEL

*No animal origin materials used in the processing of these products. Contains no animal ingredients or derivatives.

†Recycling facilities for this product may not exist in your area

Natean was created by a small passionate team of scientists and herbalists on a mission to give you the best of what nature and science can offer, while minimizing our impact to the planet. Our toothpastes expertly balance powerful, scientifically studied ingredients with botanicals for a clean you can feel, and a clean you can feel good about.

NATEAN-INSPIRED BY NATURE AND DESIGNED TO BE CLEAN

WHITENS TEETH AND LEAVES YOUR MOUTH FEELING CLEAN AND FRESH

- Our blend with pineapple and papaya extracts, and silica removes stains and whitens teeth
- Contains Fluoride to fight cavities
- Helps control tartar build-up with twice daily brushing

BPA-FREE TUBE

Tube contains post consumer recycled plastic

Recycleable carton, tube & cap

Distributed by: Alacer Corp.Carlisle, PA 17013

Made in Taiwan © 2021 Alacer Corp.

www.nateantoothpaste.com

Principal Display Panel

NDC 0135-1200-03

Natean

FLUORIDE TOOTHPASTE

NATURAL FLAVORS

AND SWEETENERS

NON-GMO / GLUTEN-FREE

NO ARTIFICIAL PRESERVATIVES,

COLORS, DYES

NO SLS/TRICLOSAN

VEGAN-FRIENDLY*

INFUSED WITH

BOTANICALS

FLUORIDE

CLEAN + WHITEN

CLEAN MINT

NET WT 4.7 OZ (133g)

60000000133573 Front Carton